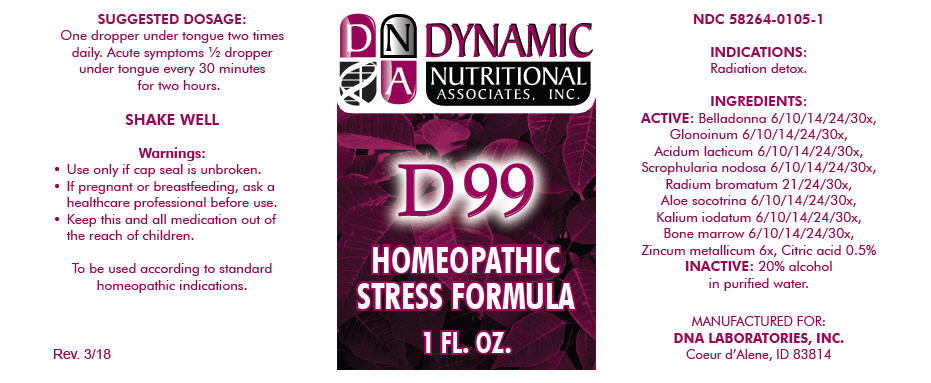 DRUG LABEL: D-99
NDC: 58264-0105 | Form: SOLUTION
Manufacturer: DNA Labs, Inc.
Category: homeopathic | Type: HUMAN OTC DRUG LABEL
Date: 20250113

ACTIVE INGREDIENTS: ATROPA BELLADONNA 6 [hp_X]/1 mL; NITROGLYCERIN 6 [hp_X]/1 mL; LACTIC ACID, UNSPECIFIED FORM 6 [hp_X]/1 mL; SCROPHULARIA NODOSA 6 [hp_X]/1 mL; ALOE 6 [hp_X]/1 mL; RADIUM BROMIDE 21 [hp_X]/1 mL; POTASSIUM IODIDE 6 [hp_X]/1 mL; SUS SCROFA BONE MARROW 6 [hp_X]/1 mL; ZINC 6 [hp_X]/1 mL; CITRIC ACID MONOHYDRATE 2 [hp_X]/1 mL
INACTIVE INGREDIENTS: ALCOHOL; WATER

D-99

NDC 58264-0105-1

INDICATIONS

PURPOSE

Radiation detox.

INGREDIENTS

ACTIVE

Belladonna 6/10/14/24/30x, Glonoinum 6/10/14/24/30x, Acidum lacticum 6/10/14/24/30x, Scrophularia nodosa 6/10/14/24/30x, Radium bromatum 21/24/30x, Aloe socotrina 6/10/14/24/30x, Kalium iodatum 6/10/14/24/30x, Bone marrow 6/10/14/24/30x, Zincum metallicum 6x, Citric acid 0.5%

INACTIVE

20% alcohol in purified water.

SUGGESTED DOSAGE

One dropper under tongue two times daily. Acute symptoms ½ dropper under tongue every 30 minutes for two hours.

STORAGE AND HANDLING

SHAKE WELL

Warnings

- Use only if cap seal is unbroken.

PREGNANCY OR BREAST FEEDING

- If pregnant or breastfeeding, ask a healthcare professional before use.

KEEP OUT OF REACH OF CHILDREN

- Keep this and all medication out of the reach of children.

To be used according to standard homeopathic indications.

PRINCIPAL DISPLAY PANEL - 1 FL. OZ. Bottle Label

DYNAMIC
NUTRITIONAL
ASSOCIATES, INC.

D 99

HOMEOPATHIC
STRESS FORMULA

1 FL. OZ.